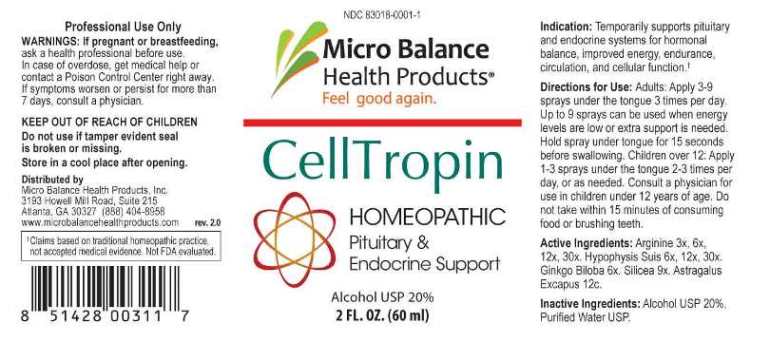 DRUG LABEL: CellTropin
NDC: 83018-0001 | Form: LIQUID
Manufacturer: Micro Balance Health Products LLC
Category: homeopathic | Type: HUMAN OTC DRUG LABEL
Date: 20230214

ACTIVE INGREDIENTS: ARGININE 3 [hp_X]/1 mL; GINKGO 6 [hp_X]/1 mL; SUS SCROFA PITUITARY GLAND 6 [hp_X]/1 mL; SILICON DIOXIDE 9 [hp_X]/1 mL; ASTRAGALUS EXSCAPUS WHOLE 12 [hp_C]/1 mL
INACTIVE INGREDIENTS: WATER; ALCOHOL

DRUG FACTS:

ACTIVE INGREDIENTS:

Arginine 3X, 6X, 12X, 30X, Ginkgo Biloba 6X, Hypophysis Suis 6X, 12X, 30X, Silicea 9X, Astragalus Excapus 12C.

PURPOSE:

Temporarily supports pituitary and endocrine systems for hormonal balance, improved energy, endurance, circulation, and cellular function. †

†Claims based on traditional homeopathic practice, not accepted medical evidence. Not FDA evaluated.

WARNINGS:

Professional Use Only

If pregnant or breast-feeding, ask a health professional before use.

In case of overdose, get medical help or contact a Poison Control Center right away.

If symptoms worsen or persist for more than 7 days, consult a physician.

KEEP OUT OF REACH OF CHILDREN

Do not use if tamper evident seal is broken or missing.

Store in a cool place after opening

KEEP OUT OF REACH OF CHILDREN:

In case of overdose, get medical help or contact a Poison Control Center right away.

DIRECTIONS:

Adults: Apply 3-9 sprays under the tongue 3 times per day. Up to 9 sprays can be used when energy levels are low or extra support is needed. Hold spray under tongue for 15 seconds before swallowing.

Children over 12: Apply 1-3 sprays under the tongue 2-3 times per day, or as needed. Consult a physician for use in children under 12 years of age. Do not take within 15 minutes of consuming food or brushing teeth.

INDICATIONS:

Temporarily supports pituitary and endocrine systems for hormonal balance, improved energy, endurance, circulation, and cellular function. †

†Claims based on traditional homeopathic practice, not accepted medical evidence. Not FDA evaluated.

INACTIVE INGREDIENTS:

Alcohol USP 20%, Purified Water USP.

QUESTIONS:

Distributed by

Micro Balance Health Products, Inc.

3193 Howell Mill Road, Suite 215

Atlanta, GA 30327 (888) 404-8958

www.microbalancehealthproducts.com

PACKAGE LABEL DISPLAY:

NDC 83018-0001-1

Micro Balance

Health Products®

Feel good again.

CellTropin

HOMEOPATHIC

Pituitary &

Endocrine Support

2FL. OZ. (60 ml)